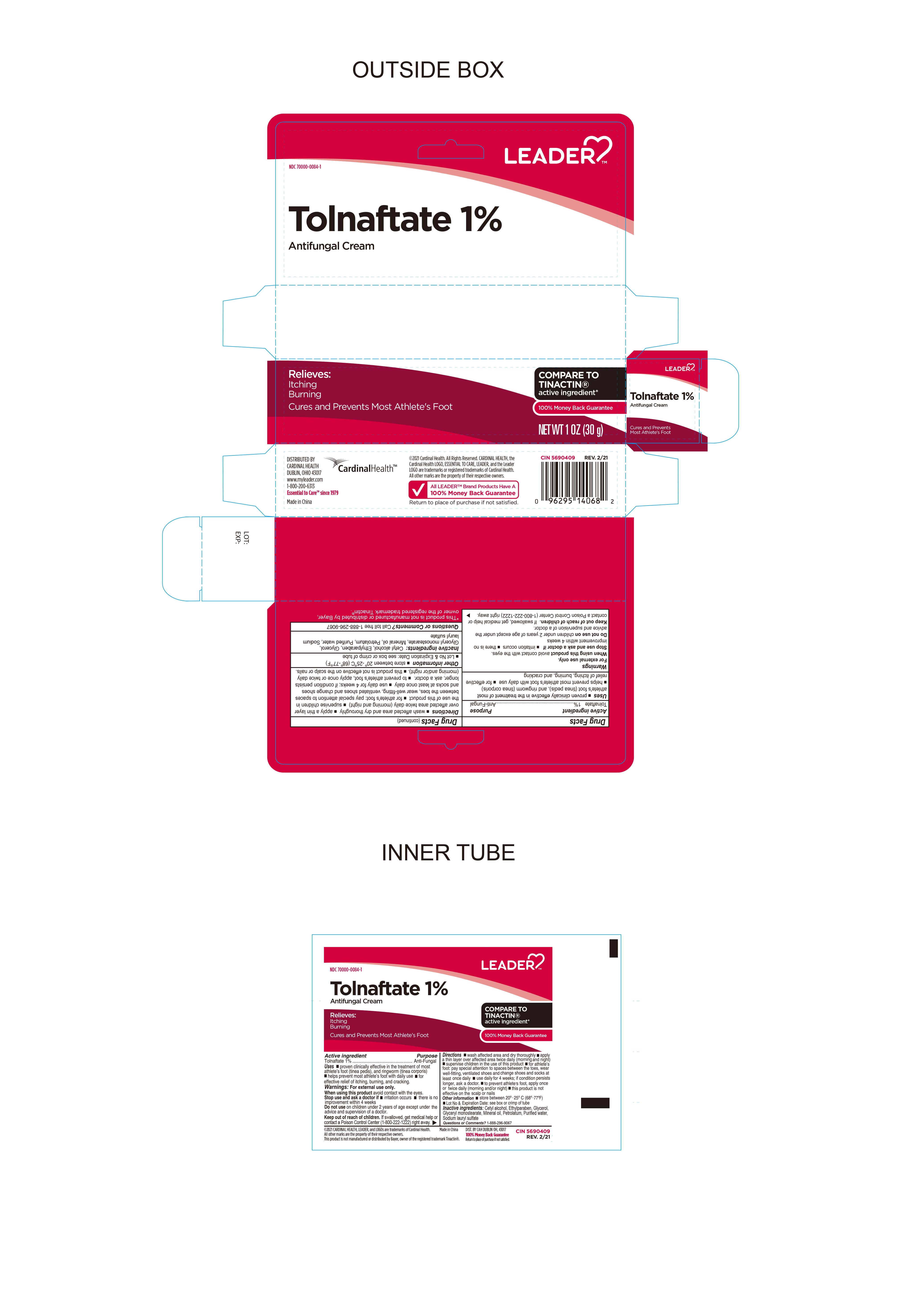 DRUG LABEL: Tolnaftate Cream 1% ANTIFUNGAL
NDC: 70000-0084 | Form: CREAM
Manufacturer: CARDINAL HEALTH 110 dba LEADER
Category: otc | Type: HUMAN OTC DRUG LABEL
Date: 20251202

ACTIVE INGREDIENTS: TOLNAFTATE 1 g/100 g
INACTIVE INGREDIENTS: CETYL ALCOHOL; ETHYLPARABEN; GLYCERIN; MINERAL OIL; GLYCERYL MONOSTEARATE; PETROLATUM; WATER; SODIUM LAURYL SULFATE

Leader Tolnaftate Cream 1% ANTIFUNGAL CREAM

Active ingredient

Tolnaftate 1%

Purpose

Anti-Fungal

Keep out of reach of children. If swallowed, get medical help or contact a Poison Control Center (1-800-222-1222) right away.

Uses

● proven clinically effective in the treatment of most athlete's foot (tinea pedis), and ringworm (tinea corporis) ● helps prevent most athlete's foot with daily use ● for effective relief of itching, burning and cracking.

Warnings

For external use only.

When using this product avoid contact with the eyes.

Stop use and ask a doctor if ● irritation occurs ● there is no improvement within 4 weeks

Do not use on children under 2 years of age except under the advice and supervision of a doctor.

Directions

● wash affected area and dry thoroughly

● apply a thin layer over affected area twice daily (morning and night)

● supervise children in the use of this product

● for athlete’s foot: pay special attention to spaces between the toes, wear well-fitting ventilated shoes and change shoes and socks at least once daily.

● use daily for 4 weeks; if conditions persists longer, ask a doctor.

● to prevent athlete's foot, apply once or twice daily (morning and/or night)

● this product is not effective on the scalp or nails.

Inactive ingredients

Cetostearyl alcohol, ethylparaben, glycerol, light mineral oil, monostearin, petrolatum, purified water, sodium dodecyl sulfate

Other information

● store between 20° to 25°C (68° to 77°F) ● Lot No & Expiration Date: See box or crimp of tube.

Questions or Comments?

1-888-296-9067

Distributed By

Distrubuted By Cardinal Health

Dublin, Ohio 43017

www.myleader.com

1-800-200-6313

Essential to Care since 1979

Made in China

2021 Cardinal Health. All rights reserved Cardinal Health, the Cardinal Health LOGO, ESSENTIAL TO CARE and Leader LOGO are trademarks or registered Trademarks of Cardinal Health. All other marks are the property of their respective owners.

All Leader Brand products have a 100% Money Back Guarantee

This product is not manufactured or distributed by Bayer, owner of the registered trademark Tinactin.